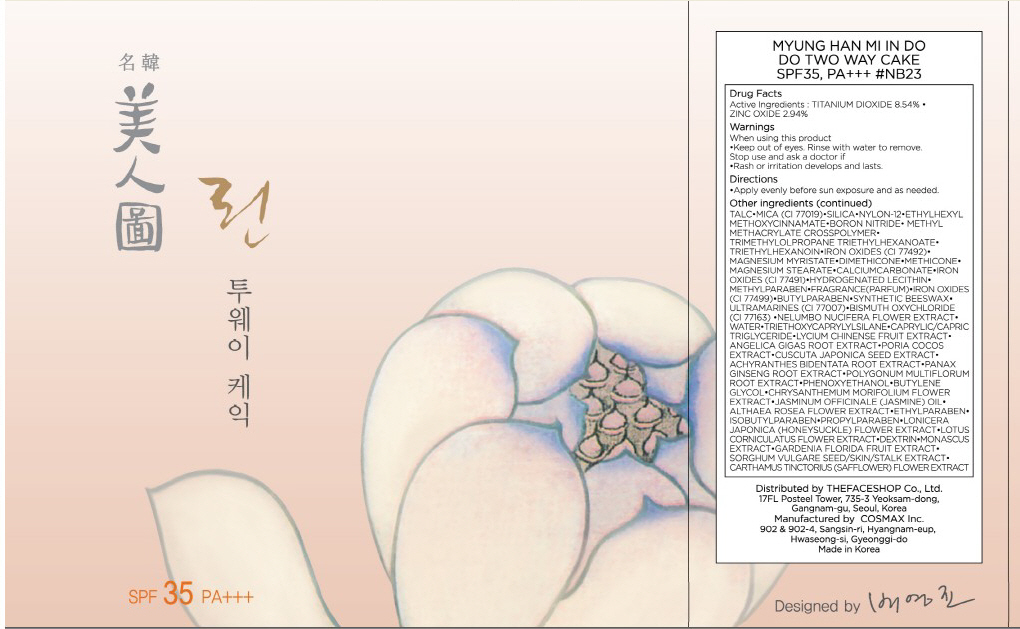 DRUG LABEL: MYUNG HAN MI IN DO TWO WAY CAKE
NDC: 51523-018 | Form: POWDER
Manufacturer: THEFACESHOP CO., LTD.
Category: otc | Type: HUMAN OTC DRUG LABEL
Date: 20100714

ACTIVE INGREDIENTS: TITANIUM DIOXIDE 1.02 g/12 g; ZINC OXIDE 0.35 g/12 g

Drug Facts

Active Ingredients: TITANIUM DIOXIDE, ZINC OXIDE

Inactive Ingredients:
WATER, TALC, MICA(CI 77019), SILICA, NYLON-12, ETHYLHEXYL METHOXYCINNAMATE, BORON NITRIDE, METHYL METHACRYLATE CROSSPOLYMER, TRIMETHYLOLPROPANE TRIETHYLHEXANOATE, TRIETHYLHEXANOIN, IRON OXIDES(CI 77492), MAGNESIUM MYRISTATE, DIMETHICONE, METHICONE, MAGNESIUM STEARATE, CALCIUM CARBONATE, IRON OXIDES(CI 77491), HYDROGENATED LECITHIN, METHYLPARABEN, FRAGRANCE, IRON OXIDES(CI 77499), BUTYLPARABEN, SYNTHETIC BEESWAX, ULTRAMARINES(CI 77007), BISMUTH OXYCHLORIDE(CI 77163), NELUMBO NUCIFERA FLOWER EXTRACT, TRIETHOXYCAPRYLYLSILANE, CAPRYLIC/CAPRIC TRIGLYCERIDE, LYCIUM CHINENSE FRUIT EXTRACT, ANGELICA GIGAS ROOT EXTRACT, PORIA COCOS EXTRACT, CUSCUTA JAPONICA SEED EXTRACT, ACHYRANTHES BIDENTATA ROOT EXTRACT, PANAX GINSENG ROOT EXTRACT, POLYGONUM MULTIFLORUM ROOT EXTRACT, PHENOXYETHANOL, BUTYLENE GLYCOL, CHRYSANTHEMUM MORIFOLIUM FLOWER EXTRACT, JASMINUM OFFICINALE (JASMINE) OIL, ALTHAEA ROSEA FLOWER EXTRACT, ETHYLPARABEN, ISOBUTYLPARABEN, PROPYLPARABEN, LONICERA JAPONICA (HONEYSUCKLE) FLOWER EXTRACT, LOTUS CORNICULATUS FLOWER EXTRACT, DEXTRIN, MONASCUS EXTRACT, GARDENIA FLORIDA, FRUIT EXTRACT, SORGHUM VULGARE SEED/SKIN/STALK EXTRACT, CARTHAMUS TINCTORIUS (SAFFLOWER) FLOWER EXTRACT

Warnings:
When using this product
Keep out of eyes. Rinse with water to remove.
Stop use and ask a doctor if
Rash or irritation develops and lasts.
Directions:
Apply evenly before sun exposure and as needed.